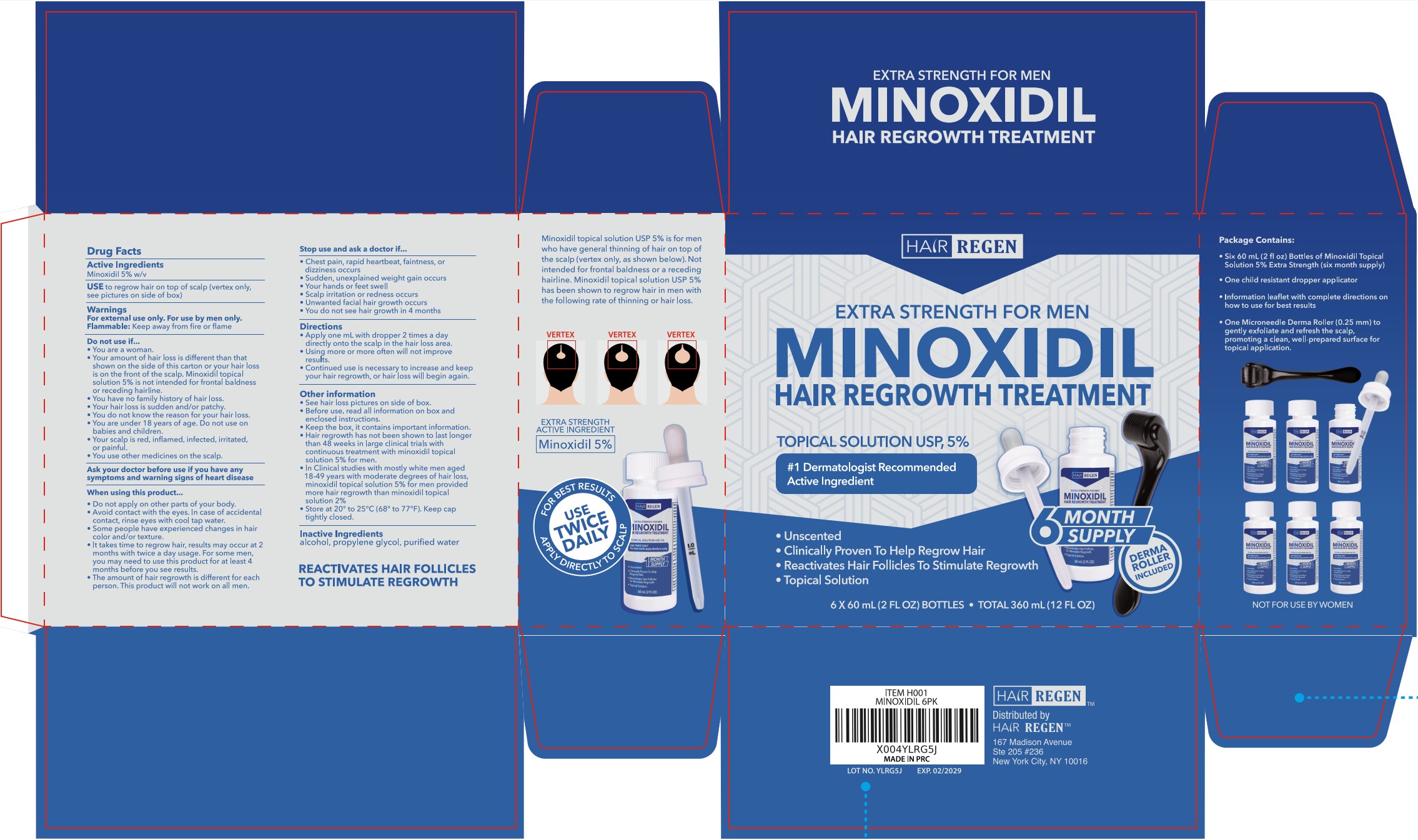 DRUG LABEL: Hair-Regen Hair Growth Treatment Derma Roller Included
NDC: 84232-021 | Form: LIQUID
Manufacturer: Yiwu Yizhou Trading Co., Ltd
Category: otc | Type: HUMAN OTC DRUG LABEL
Date: 20260206

ACTIVE INGREDIENTS: MINOXIDIL 5 g/100 mL
INACTIVE INGREDIENTS: ALCOHOL; PROPYLENE GLYCOL; WATER

Minoxidil 5%, Hair-Regen Derma Roller Included, 60mL*6Bottle

Active Ingredients

Minoxidil 5% w/v

Purpose

Hair Regrowth Treatment

USE

to regrow hair on top of scalp (vertex only, see pictures on side of box)

Warnings

For external use only. For use by men only.

Flammable: Keep away from fire or flame.

Do not use if...

- You are a woman.
- Your amount of hair loss is different than that shown on the side of this carton or your hair loss is on the front of the scalp. Minoxidil topical solution 5% is not intended for frontal baldness or receding hairline.
- You have no family history of hair loss.
- Your hair loss is sudden and/or patchy.
- You do not know the reason for your hair loss.
- You are under 18 years of age. Do not use on babies and children.
- Your scalp is red, inflamed, infected, rritated, or painful.
- You use other medicines on the scalp.

ASK DOCTOR

Ask your doctor before use if you have any symptoms and warning signs of heart disease.

When using this product...

- Do not apply on other parts of your body.
- Avoid contact with the eyes. In case of accidental contact, rinse eyes with cool tap water.
- Some people have experienced changes in hair color and/or texture.
- It takes time to regrow hair, results may occur at 2 months with twice a day usage. For some men, you may need to use this product for at least 4 months before you see results.
- The amount of hair regrowth is different for each person. This product will not work on all men.

Stop use and ask doctor if...

- Chest pain, rapid heartbeat, faintness, or dizziness occurs
- Sudden, unexplained weight gain occurs
- Your hands or feet swell
- Scalp rritation or redness occurs
- Unwanted facial hair growth occurs
- You do not see hair growth in 4 months

Do not use it on babies and children.

Directions

- Apply one mL with dropper 2 times a day directly onto the scalp in the hair loss area.
- Using more or more often will not improve results.
- Continued use is necessary to increase and keep your hair regrowth, or hair loss will begin again.

Other information

- See hair loss pictures on side of box.
- Before use, read all information on box and enclosed instructions.
- Keep the box, it contains important information.
- Hair regrowth has not been shown to last longer than 48 weeks in large clinical trials with continuous treatment with minoxidil topical solution 5% for men.
- In Clinical studies with mostly white men aged 18-49 years with moderate degrees of hair loss, minoxidil topical solution 5% for men provided more hair regrowth than minoxidil topical solution 2%
- Store at 20° to 25℃ (68° to 77℉). Keep cap tightly closed.

STORAGE AND HANDLING

Store at 20° to 25℃ (68° to 77℉). Keep cap tightly closed.

Inactive Ingredients

alcohol, propylene glycol, purified water